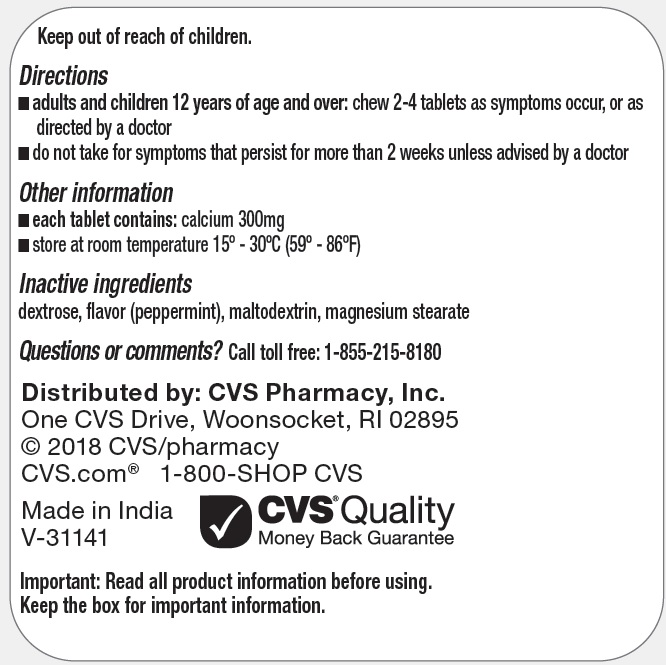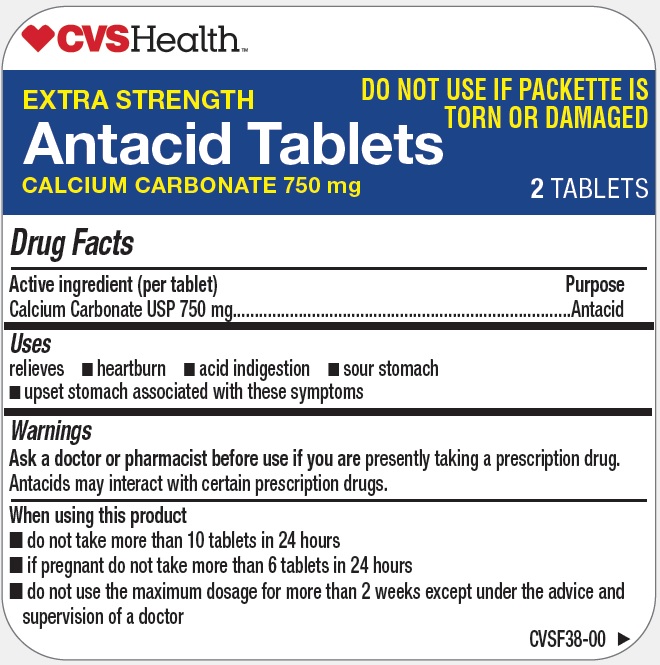 DRUG LABEL: Extra Strength Antacid
NDC: 69842-396 | Form: TABLET, CHEWABLE
Manufacturer: CVS PHARMACY, INC.
Category: otc | Type: HUMAN OTC DRUG LABEL
Date: 20171213

ACTIVE INGREDIENTS: CALCIUM CARBONATE 750 mg/1 1
INACTIVE INGREDIENTS: DEXTROSE; PEPPERMINT; MALTODEXTRIN; MAGNESIUM STEARATE

Extra Strength Antacid Tablets

Active ingredient (per tablet)

Calcium Carbonate USP 750 mg

Purpose

Antacid

Uses

relieves

- heartburn
- acid indigestion
- sour stomach
- upset stomach associated with these symptoms

Warnings

Ask a doctor or pharmacist before use if you are

presently taking a prescription drug. Antacids may interact with certain prescription drugs.

When using this product

- do not take more than 10 tablets in 24 hours
- if pregnant do not take more than 6 tablets in 24 hours
- do not use the maximum dosage for more than 2 weeks except under the advice and supervision of a doctor

Keep out of reach of children.

Directions

- adults and children 12 years of age and over: chew 2 - 4 tablets as symptoms occur, or as directed by a doctor
- do not take for symptoms that persist for more than 2 weeks unless advised by a doctor

Other information

- each tablet contains: calcium 300 mg
- store at room temperature 15° - 30°C (59° - 86°F)

Inactive ingredients

dextrose, flavor (peppermint), maltodextrin, magnesium stearate

Questions or comments?

Call toll free: 1-855-215-8180

PRINCIPAL DISPLAY PANEL

Extra Strength Antacid Tablets

30 Tablets 15 Pouches (2 Tablets per Pouch)

NDC 69842-396-54